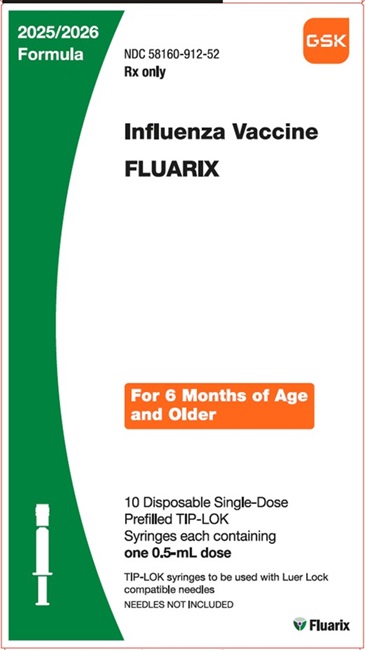 DRUG LABEL: FLUARIX
NDC: 58160-912 | Form: SUSPENSION
Manufacturer: GlaxoSmithKline Biologicals SA
Category: other | Type: VACCINE LABEL
Date: 20250701

ACTIVE INGREDIENTS: INFLUENZA A VIRUS A/VICTORIA/4897/2022 IVR-238 (H1N1) ANTIGEN (FORMALDEHYDE INACTIVATED) 15 ug/0.5 mL; INFLUENZA A VIRUS A/THAILAND/8/2022 IVR-237 (H3N2) ANTIGEN (FORMALDEHYDE INACTIVATED) 15 ug/0.5 mL; INFLUENZA B VIRUS B/AUSTRIA/1359417/2021 BVR-26 ANTIGEN (FORMALDEHYDE INACTIVATED) 15 ug/0.5 mL
INACTIVE INGREDIENTS: OCTOXYNOL-9; .ALPHA.-TOCOPHEROL SUCCINATE, D-; POLYSORBATE 80; POTASSIUM CHLORIDE; SODIUM CHLORIDE

HIGHLIGHTS OF PRESCRIBING INFORMATION

These highlights do not include all the information needed to use FLUARIX safely and effectively. See full prescribing information for FLUARIX.
FLUARIX (Influenza Vaccine)
Injectable Suspension, for Intramuscular Use
2025-2026 Formula
Initial U.S. Approval: 2005

1 INDICATIONS AND USAGE

FLUARIX is a vaccine indicated for active immunization for the prevention of disease caused by influenza A subtype viruses and type B virus contained in the vaccine. FLUARIX is approved for use in persons aged 6 months and older. (1)

2 DOSAGE AND ADMINISTRATION

For intramuscular use. (2)

Age | Vaccination Status | Dose and Schedule
6 months through 8 years | Not previously vaccinated with influenza vaccine | Two doses (0.5 mL each) at least 4 weeks apart (2.1)
6 months through 8 years | Vaccinated with influenza vaccine in a previous season | One or 2 dosesa (0.5 mL each) (2.1)
9 years and older | Not applicable | One 0.5‑mL dose (2.1)
a One dose or 2 doses (0.5 mL each) depending on vaccination history as per the annual Advisory Committee on Immunization Practices (ACIP) recommendation on prevention and control of seasonal influenza with vaccines. If 2 doses, administer each 0.5‑mL dose at least 4 weeks apart. (2.1)

3 DOSAGE FORMS AND STRENGTHS

FLUARIX is an injectable suspension. A single dose is 0.5 mL. (3)

4 CONTRAINDICATIONS

Do not administer FLUARIX to anyone with a history of severe allergic reactions (e.g., anaphylaxis) to any component of the vaccine, including egg protein, or following a previous dose of any influenza vaccine. (4, 11)

5 WARNINGS AND PRECAUTIONS

- If Guillain-Barré syndrome has occurred within 6 weeks of receipt of a prior influenza vaccine, the decision to give FLUARIX should be based on careful consideration of potential benefits and risks. (5.1)
- Syncope (fainting) can occur in association with administration of injectable vaccines, including FLUARIX. Procedures should be in place to avoid injury from fainting. (5.2)

6 ADVERSE REACTIONS

- In adults who received FLUARIX, the most common (≥10%) solicited local adverse reactions were pain (55%) and redness (18%); the most common systemic adverse reactions were muscle aches (23%), fatigue (20%), and headache (19%). (6.1)
- In children aged 5 through 17 years who received FLUARIX, the most common (≥10%) solicited local adverse reactions were pain (56%), redness (18%), and swelling (14%); the most common systemic adverse reactions were muscle aches (29%), fatigue (20%), and headache (15%). (6.1)
- In children aged 3 through 4 years who received FLUARIX, the most common (≥10%) solicited local adverse reactions were pain (35%), redness (23%), and swelling (14%); the most common systemic adverse reactions were irritability (21%), loss of appetite (13%), and drowsiness (13%). (6.1)
- In children aged 6 through 35 months who received FLUARIX QUADRIVALENT, the most common (≥10%) solicited local adverse reactions were pain (17%) and redness (13%); the most common systemic adverse reactions were irritability (16%), loss of appetite (14%), and drowsiness (13%). (6.1)

To report SUSPECTED ADVERSE REACTIONS, contact GlaxoSmithKline at 1-888-825-5249 or VAERS at 1-800-822-7967 or www.vaers.hhs.gov.

8 USE IN SPECIFIC POPULATIONS

- Geriatric Use: Antibody responses were lower in geriatric subjects who received FLUARIX than in younger subjects. (8.5)

FULL PRESCRIBING INFORMATION

1 INDICATIONS AND USAGE

FLUARIX is indicated for active immunization for the prevention of disease caused by influenza A subtype viruses and type B virus contained in the vaccine [see Description (11)]. FLUARIX is approved for use in persons aged 6 months and older.

2 DOSAGE AND ADMINISTRATION

For intramuscular use.

2.1 Dosage and Schedule

The dose and schedule for FLUARIX are presented in Table 1.

Table 1. FLUARIX: Dosing
Age | Vaccination Status | Dose and Schedule
6 months through 8 years | Not previously vaccinated with influenza vaccine | Two doses (0.5 mL each) at least 4 weeks apart
6 months through 8 years | Vaccinated with influenza vaccine in a previous season | One or 2 dosesa (0.5 mL each)
9 years and older | Not applicable | One 0.5‑mL dose
a One dose or 2 doses (0.5 mL each) depending on vaccination history as per the annual Advisory Committee on Immunization Practices (ACIP) recommendation on prevention and control of seasonal influenza with vaccines. If 2 doses, administer each 0.5‑mL dose at least 4 weeks apart.

2.2 Administration Instructions

Shake well before administration. Parenteral drug products should be inspected visually for particulate matter and discoloration prior to administration, whenever solution and container permit. If either of these conditions exists, the vaccine should not be administered.

Attach a sterile needle to the prefilled syringe and administer intramuscularly.

3 DOSAGE FORMS AND STRENGTHS

FLUARIX is an injectable suspension. A single dose is 0.5 mL.

4 CONTRAINDICATIONS

Do not administer FLUARIX to anyone with a history of severe allergic reactions (e.g., anaphylaxis) to any component of the vaccine, including egg protein, or following a previous administration of any influenza vaccine [see Description (11)].

5 WARNINGS AND PRECAUTIONS

5.1 Guillain-Barré Syndrome

If Guillain‑Barré syndrome (GBS) has occurred within 6 weeks of receipt of a prior influenza vaccine, the decision to give FLUARIX should be based on careful consideration of the potential benefits and risks.

The 1976 swine influenza vaccine was associated with an increased frequency of GBS. Evidence for a causal relation of GBS with subsequent vaccines prepared from other influenza viruses is inconclusive. If influenza vaccine does pose a risk, it is probably slightly more than 1 additional case/1 million persons vaccinated.

5.2 Syncope

Syncope (fainting) may occur in association with administration of injectable vaccines, including FLUARIX. Procedures should be in place to avoid injury from fainting.

5.3 Preventing and Managing Allergic Vaccine Reactions

Appropriate medical treatment must be immediately available to manage potential anaphylactic reactions following administration of FLUARIX.

5.4 Altered Immunocompetence

If FLUARIX is administered to immunosuppressed persons, including individuals receiving immunosuppressive therapy, the immune response may be lower than in immunocompetent persons.

5.5 Limitations of Vaccine Effectiveness

Vaccination with FLUARIX may not protect all susceptible individuals.

6 ADVERSE REACTIONS

The safety experience with FLUARIX QUADRIVALENT is relevant to FLUARIX because both vaccines are manufactured using the same process and have overlapping compositions.

In adults who received FLUARIX in a randomized, placebo-controlled study, the most common (≥10%) solicited local adverse reactions were pain (55%) and redness (18%). The most common systemic adverse reactions were muscle aches (23%), fatigue (20%), and headache (19%).

In children aged 5 through 17 years who received FLUARIX, the most common (≥10%) solicited local adverse reactions were pain (56%), redness (18%), and swelling (14%). The most common systemic adverse reactions were muscle aches (29%), fatigue (20%), and headache (15%).

In children aged 3 through 4 years who received FLUARIX, the most common (≥10%) solicited local adverse reactions were pain (35%), redness (23%), and swelling (14%). The most common systemic adverse reactions were irritability (21%), loss of appetite (13%), and drowsiness (13%).

In children aged 6 through 35 months who received FLUARIX QUADRIVALENT, the most common (≥10%) solicited local adverse reactions were pain (17%) and redness (13%). The most common (≥10%) systemic adverse reactions were irritability (16%), loss of appetite (14%), and drowsiness (13%).

6.1 Clinical Trials Experience

Because clinical trials are conducted under widely varying conditions, adverse reaction rates observed in the clinical trials of a vaccine cannot be directly compared with rates in the clinical trials of another vaccine and may not reflect the rates observed in practice. There is the possibility that broad use of FLUARIX could reveal adverse reactions not observed in clinical trials.

FLUARIX has been administered to 10,317 individuals aged 18 through 64 years and 606 individuals aged 65 years and older in 4 clinical trials and to 1,698 individuals aged 3 through 17 years in 1 clinical trial. FLUARIX QUADRIVALENT has been administered to 6,006 individuals aged 6 through 35 months in 1 clinical trial.

Individuals Aged 18 Years and Older

Trial 1 (NCT00100399) was a randomized, double-blind, placebo-controlled trial that evaluated a total of 952 subjects: FLUARIX (N = 760) and placebo (N = 192). The population was aged 18 through 64 years (mean: 39.1), 54% were female and 80% were white. Solicited adverse reactions were collected for 4 days (day of vaccination and the next 3 days) (Table 2). Unsolicited events that occurred within 21 days of vaccination (Day 0 to 20) were recorded using diary cards supplemented by spontaneous reports and a medical history as reported by subjects.

Table 2. FLUARIX: Incidence of Solicited Local and Systemic Adverse Reactions within 4 Daysa of Vaccination in Adults Aged 18 through 64 Yearsb (Total Vaccinated Cohort)
Adverse Reaction | FLUARIX; n = 760 % |  | Placebo; n = 192 %
Adverse Reaction | Any | Grade 3c | Any | Grade 3c
Local
Pain | 55 | 0.1 | 12 | 0
Redness | 18 | 0 | 10 | 0
Swelling | 9 | 0.1 | 6 | 0
Systemic
Muscle aches | 23 | 0.4 | 12 | 0.5
Fatigue | 20 | 0.4 | 18 | 1
Headache | 19 | 0.1 | 21 | 1
Arthralgia | 6 | 0.1 | 6 | 0.5
Shivering | 3 | 0.1 | 3 | 0
Feverd | 2 | 0 | 2 | 0
Total vaccinated cohort for safety included all vaccinated subjects for whom safety data were available.
n = Number of subjects with diary card completed.
a Four days included day of vaccination and the subsequent 3 days.
b Trial 1: NCT00100399.
c Grade 3 pain, muscle aches, fatigue, headache, arthralgia, shivering: Defined as prevented normal activity.
Grade 3 redness, swelling: Defined as >50 mm.
Grade 3 fever: Defined as >102.2°F (39.0°C).
d Fever: Defined as ≥100.4°F (38.0°C).

Unsolicited adverse events that occurred in ≥1% of recipients of FLUARIX and at a rate greater than placebo included upper respiratory tract infection (3.9% versus 2.6%), nasopharyngitis (2.5% versus 1.6%), nasal congestion (2.2% versus 2.1%), diarrhea (1.6% versus 0%), influenza-like illness (1.6% versus 0.5%), vomiting (1.4% versus 0%), and dysmenorrhea (1.3% versus 1.0%).

Trial 2 (NCT00197288) was a randomized, single-blind, active-controlled U.S. trial which evaluated subjects randomized to receive FLUARIX (N = 917) or FLUZONE (N = 910), a U.S.‑licensed trivalent, inactivated influenza vaccine (Sanofi Pasteur SA) stratified by age: 18 through 64 years and 65 years and older. In the overall population, 59% of subjects were female and 91% were white. Solicited adverse reactions were collected using diary cards for 4 days (day of vaccination and the next 3 days) (Table 3). Unsolicited events that occurred within 21 days of vaccination (Day 0 to 20) were recorded using diary cards.

Table 3. FLUARIX: Incidence of Solicited Local and Systemic Adverse Reactions within 4 Daysa of Vaccination in Adultsb(Total Vaccinated Cohort)
 | Aged 18 through 64 Years |  |  |  | Aged 65 Years and Older
Adverse Reaction | FLUARIX; n = 315; % |  | Comparator; n = 314; % |  | FLUARIX; n = 601-602; % |  | Comparator; n = 596; %
Adverse Reaction | Any | Grade 3c | Any | Grade 3c | Any | Grade 3c | Any | Grade 3c
Local
Pain | 48 | 0.3 | 53 | 0.3 | 19 | 0 | 18 | 0
Redness | 13 | 0 | 16 | 1 | 11 | 0.2 | 13 | 0.7
Swelling | 9 | 0 | 11 | 2 | 6 | 0 | 9 | 0.7
Systemic
Fatigue | 21 | 0.3 | 18 | 0.6 | 9 | 0.3 | 10 | 0.7
Headache | 20 | 0.3 | 21 | 1 | 8 | 0.3 | 8 | 0.3
Muscle aches | 16 | 0 | 13 | 1 | 7 | 0.3 | 7 | 0
Arthralgia | 9 | 0 | 9 | 0.6 | 6 | 0.5 | 5 | 0.2
Shivering | 3 | 0 | 5 | 0 | 2 | 0.2 | 2 | 0
Feverd | 3 | 0 | 1 | 0 | 2 | 0 | 0.5 | 0
Total vaccinated cohort for safety included all vaccinated subjects for whom safety data were available.
n = Number of subjects with diary card completed.
a Four days included day of vaccination and the subsequent 3 days.
b Trial 2: NCT00197288. The active control was FLUZONE, a U.S.-licensed trivalent, inactivated influenza vaccine (Sanofi Pasteur Inc.).
c Grade 3 pain, muscle aches, fatigue, headache, arthralgia, shivering: Defined as prevented normal activity.
Grade 3 redness, swelling: Defined as >50 mm.
Grade 3 fever: Defined as >102.2°F (39.0°C).
d Fever: Defined as ≥99.5°F (37.5°C).

Unsolicited adverse events that occurred in ≥1% of all recipients of FLUARIX or the comparator influenza vaccine in the 21-day post-vaccination period included headache (2.8% versus 2.3%), back pain (1.5% versus 0.4%), pain in extremity (1.2% versus 0.7%), pharyngolaryngeal pain (1.2% versus 0.9%), cough (1.1% versus 0.9%), fatigue (1.1% versus 0.7%), nasopharyngitis (1.0% versus 1.3%), nausea (0.4% versus 1.0%), arthralgia (0.3% versus 1.0%), and injection site pruritus (0.2% versus 1.0%).

Trial 3 (NCT00363870) was a double-blind, placebo-controlled trial in subjects aged 18 through 64 years randomized (2:1) to receive FLUARIX (N = 5,103) or placebo (N = 2,549) which was conducted to evaluate the efficacy of FLUARIX. In the total population, 60% were female and 99.9% were white. In a subset (FLUARIX [N = 305] and placebo [N = 155]), unsolicited events that occurred within 21 days of vaccination (Day 0 to 20) were recorded on diary cards. The percentage of subjects reporting at least one unsolicited event was similar among the groups (24.3% for FLUARIX and 22.6% for placebo). Unsolicited adverse events that occurred in ≥1% of recipients of FLUARIX and at a rate greater than placebo included injection site pain (5.2% versus 1.3%), dysmenorrhea (1.3% versus 0.6%), and migraine (1.0% versus 0.0%).

Serious Adverse Events: In 4 clinical trials in adults (N = 10,923), there was a single case of anaphylaxis reported with FLUARIX (<0.01%).

Incidence of Adverse Events Reported in ≥1% of Subjects in Non-US Clinical Trials: The following additional adverse events have been observed in adults in 3 additional non-US clinical trials with FLUARIX. No adverse events were observed at an incidence of >10%.

General Disorders and Administration Site Conditions: Injection site ecchymosis, injection site induration, malaise.

Infections and Infestations: Rhinitis.

Musculoskeletal and Connective Tissue Disorders: Musculoskeletal pain, neck pain.

Skin and Subcutaneous Tissue Disorders: Sweating.

In a clinical trial (NCT01204671) in which 3,036 adults (18 years of age and older) received FLUARIX QUADRIVALENT, the unsolicited adverse reactions that occurred most frequently (≥ 0.1%) following administration of FLUARIX QUADRIVALENT included dizziness, injection site hematoma, injection site pruritus, and rash.

Individuals Aged 6 Months through 17 Years

Trial 4 (NCT00383123) was a single-blind, active-controlled U.S. trial which evaluated subjects aged 6 months through 17 years who received FLUARIX (N = 2,081) or FLUZONE (N = 1,173), a U.S.‑licensed trivalent, inactivated influenza vaccine (Sanofi Pasteur SA). Children aged 6 months through 8 years with no history of influenza vaccination received 2 doses approximately 28 days apart. Children aged 6 months through 8 years with a history of influenza vaccination and children aged 9 years and older received 1 dose. Children aged 6 months through 35 months received 0.25 mL of FLUARIX (not an approved dose of FLUARIX) or comparator influenza vaccine, and children aged 3 years and older received 0.5 mL of FLUARIX or comparator influenza vaccine.

Trial subjects were aged 6 months through 17 years and 49% were female; 68% were white, 18% were black, 3% were Asian, and 11% were of other racial/ethnic groups.

Solicited local and systemic adverse reactions were collected using diary cards for 4 days (day of vaccination and the next 3 days). Unsolicited adverse events that occurred within 28 days of vaccination (Day 0 to 27) after the first vaccination in all subjects and 21 days (Day 0 to 20) after the second vaccination in unprimed subjects were recorded using diary cards.

The frequencies of solicited adverse reactions for children aged 3 years through 4 years and for children aged 5 years through 17 years were similar for FLUARIX and the comparator vaccine (Table 4).

Table 4. FLUARIX: Incidence of Solicited Local and Systemic Adverse Reactions within 4 Daysa of First Vaccination in Children Aged 3 through 17 Yearsb (Total Vaccinated Cohort)
 | Aged 3 through 4 Years |  |  |  | Aged 5 through 17 Years
Adverse Reaction | FLUARIX; n = 350; % |  | Comparator; n = 341; % |  | FLUARIX; n = 1,348; % |  | Comparator; n = 451; %
Adverse Reaction | Any | Grade 3c | Any | Grade 3c | Any | Grade 3c | Any | Grade 3c
Local
Pain | 35 | 2 | 38 | 1 | 56 | 0.8 | 56 | 0.7
Redness | 23 | 0.3 | 20 | 0 | 18 | 1 | 16 | 0.7
Swelling | 14 | 0 | 13 | 0 | 14 | 2 | 13 | 0.7
Systemic
Irritability | 21 | 0.9 | 22 | 0 | – | – | – | –
Loss of appetite | 13 | 0.9 | 15 | 0.9 | – | – | – | –
Drowsiness | 13 | 0.6 | 20 | 0.9 | – | – | – | –
Feverd | 7 | 1 | 8 | 2 | 4 | 0.3 | 3 | 0.2
Muscle aches | – | – | – | – | 29 | 0.4 | 29 | 0.4
Fatigue | – | – | – | – | 20 | 1 | 19 | 1
Headache | – | – | – | – | 15 | 0.5 | 16 | 0.9
Arthralgia | – | – | – | – | 6 | 0.1 | 6 | 0.2
Shivering | – | – | – | – | 3 | 0.1 | 4 | 0.2
Total vaccinated cohort for safety included all vaccinated subjects for whom safety data were available.
n = Number of subjects with diary card completed.
a Four days included day of vaccination and the subsequent 3 days.
b Trial 4: NCT00383123. The active control was FLUZONE, a U.S.-licensed trivalent, inactivated influenza vaccine (Sanofi Pasteur Inc.).
c Grade 3 pain, irritability, loss of appetite, drowsiness, muscle aches, fatigue, headache, arthralgia, shivering: Defined as prevented normal activity.
Grade 3 swelling, redness: Defined as >50 mm.
Grade 3 fever: Defined as >102.2°F (39.0°C).
d Fever: Defined as ≥99.5°F (37.5°C).

In children who received a second dose of FLUARIX or the comparator vaccine, the incidences of adverse reactions following the second dose were similar to those observed after the first dose.

Unsolicited adverse events that occurred in ≥1% of recipients of FLUARIX aged 6 months through 17 years included upper respiratory tract infection (5.5%), pyrexia (4.8%), cough (4.7%), vomiting (3.2%), headache (2.8%), rhinorrhea (2.7%), diarrhea (2.5%), pharyngolaryngeal pain (2.4%), nasopharyngitis (2.3%), otitis media (2.0%), nasal congestion (1.8%), upper abdominal pain (1.4%), and upper respiratory tract congestion (1.0%). The incidences of these events were similar in recipients of the comparator vaccine.

Trial 5 (NCT01439360) was a randomized, observer-blind, non-influenza vaccine-controlled trial evaluating the efficacy of FLUARIX QUADRIVALENT. In this trial, subjects aged 6 through 35 months received FLUARIX QUADRIVALENT (n = 6,006) or a control vaccine (n = 6,012). The comparator was pneumococcal 13-valent conjugate vaccine [Diphtheria CRM197 Protein] (Wyeth Pharmaceuticals, Inc.) in children younger than 12 months, HAVRIX (Hepatitis A Vaccine) in children 12 months and older with a history of influenza vaccination, or HAVRIX (Dose 1) and a varicella vaccine (U.S. Licensed Manufactured by Merck & Co., Inc. or Non-U.S. Licensed Manufactured by GlaxoSmithKline Biologicals) (Dose 2) in those with no history of influenza vaccination. Subjects were aged 6 through 35 months, and one child aged 43 months (mean age: 22 months); 51% were male; 27% were white, 45% were Asian, and 28% were of other racial/ethnic groups. Children aged 12 months and older with no history of influenza vaccination and children younger than 12 months received 2 doses of FLUARIX QUADRIVALENT or the control vaccine approximately 28 days apart. Children aged 12 months and older with a history of influenza vaccination received one dose. Solicited local adverse reactions and systemic adverse events were collected using diary cards for 7 days (day of vaccination and the next 6 days). The incidences of solicited adverse reactions are shown in Table 5.

Table 5. FLUARIX QUADRIVALENT: Incidence of Solicited Local and Systemic Adverse Reactions within 7 Daysa after First Vaccination in Children Aged 6 through 35 Monthsb (Total Vaccinated Cohort)
Adverse Reactions | FLUARIX QUADRIVALENT; % |  | Non-Influenza Active Comparatorc,d; %
Adverse Reactions | Any | Grade 3e | Any | Grade 3e
Local | n = 5,899 |  | n = 5,896
Pain | 17 | 0.4 | 18 | 0.5
Redness | 13 | 0 | 14 | 0
Swelling | 8 | 0 | 9 | 0
Systemic | n = 5,898 |  | n = 5,896
Irritability | 16 | 0.7 | 18 | 1
Loss of appetite | 14 | 1 | 15 | 1
Drowsiness | 13 | 0.7 | 14 | 0.9
Feverf | 6 | 1 | 7 | 1
Total vaccinated cohort for safety included all vaccinated subjects for whom safety data were available.
n = Number of subjects with diary card completed.
a Seven days included day of vaccination and the subsequent 6 days.
b Trial 5: NCT01439360.
c Children younger than 12 months: pneumococcal 13-valent conjugate vaccine [Diphtheria CRM197 Protein] (Wyeth Pharmaceuticals, Inc.).
d Children 12 months and older: HAVRIX (Hepatitis A Vaccine) for those with a history of influenza vaccination; or HAVRIX (Dose 1) and a varicella vaccine (U.S. Licensed Manufactured by Merck & Co., Inc. or Non-U.S. Licensed Manufactured by GlaxoSmithKline Biologicals) (Dose 2) for those with no history of influenza vaccination.
e Grade 3 pain: Defined as cried when limb was moved/spontaneously painful.
Grade 3 swelling, redness: Defined as >50 mm.
Grade 3 irritability: Defined as crying that could not be comforted/prevented normal activity. Grade 3 loss of appetite: Defined as not eating at all.
Grade 3 drowsiness: Defined as prevented normal activity. Grade 3 fever: Defined as >102.2°F (39.0°C).
f Fever: Defined as ≥100.4°F (38.0°C).

In children who received a second dose of FLUARIX QUADRIVALENT or the Non-Influenza Active Comparator vaccine, the incidences of solicited adverse reactions following the second dose were generally lower than those observed after the first dose.

Unsolicited adverse events occurring within 28 days of vaccination were reported in 44% and 45% of subjects who received FLUARIX QUADRIVALENT (n = 6,006) and the comparator vaccine (n = 6,012), respectively. Serious adverse events (SAEs) occurring during the study period (6 to 8 months) were reported in 3.6% of subjects who received FLUARIX QUADRIVALENT and in 3.3% of subjects who received the comparator vaccine.

In a clinical trial (NCT01196988) in which 915 children (3 through 17 years of age) received FLUARIX QUADRIVALENT, the related unsolicited adverse reactions that occurred most frequently (≥ 0.1%), following administration of FLUARIX QUADRIVALENT, included injection site pruritus and rash.

Concomitant Administration with Zoster Vaccine Recombinant, Adjuvanted (SHINGRIX)

In an open-label, randomized trial (NCT01954251), adults aged 50 years and older (median 63 years, range 50 to 92 years) received FLUARIX QUADRIVALENT and SHINGRIX at Month 0 and SHINGRIX at Month 2 (n = 413), or FLUARIX QUADRIVALENT at Month 0 and SHINGRIX at Months 2 and 4 (n = 415). Information about solicited local and systemic adverse reactions was collected using diary cards for 7 days (day of vaccination and the next 6 days). The rates of the solicited, systemic adverse reactions of fatigue, headache, myalgia, shivering, and fever (≥37.5oC) reported in subjects receiving FLUARIX QUADRIVALENT and SHINGRIX concomitantly were similar to those observed with SHINGRIX alone, and higher than when FLUARIX QUADRIVALENT was given alone.

6.2 Postmarketing Experience

The following adverse reactions have been identified during post approval use of FLUARIX or FLUARIX QUADRIVALENT. Because these reactions are reported voluntarily from a population of uncertain size, it is not always possible to reliably estimate their frequency or establish a causal relationship to the vaccine.

Blood and Lymphatic System Disorders

Lymphadenopathy.

Cardiac Disorders

Tachycardia.

Ear and Labyrinth Disorders

Vertigo.

Eye Disorders

Conjunctivitis, eye irritation, eye pain, eye redness, eye swelling, eyelid swelling.

Gastrointestinal Disorders

Abdominal pain or discomfort, nausea, swelling of the mouth, throat, and/or tongue.

General Disorders and Administration Site Conditions

Asthenia, chest pain, chills, influenza-like illness, feeling hot, injection site mass, injection site reaction, injection site warmth, body aches.

Immune System Disorders

Anaphylactic reaction including shock, anaphylactoid reaction, hypersensitivity, serum sickness.

Infections and Infestations

Injection site abscess, injection site cellulitis, pharyngitis, rhinitis, tonsillitis.

Musculoskeletal and Connective Tissue Disorders

Pain in extremity.

Nervous System Disorders

Convulsion, dizziness encephalomyelitis, facial palsy, facial paresis, Guillain-Barré syndrome, hypoesthesia, myelitis, neuritis, neuropathy, paresthesia, syncope.

Respiratory, Thoracic, and Mediastinal Disorders

Asthma, bronchospasm, cough, dyspnea, respiratory distress, stridor.

Skin and Subcutaneous Tissue Disorders

Angioedema, erythema, erythema multiforme, facial swelling, pruritus, rash, Stevens-Johnson syndrome, sweating, urticaria.

Vascular Disorders

Henoch-Schönlein purpura, vasculitis.

8 USE IN SPECIFIC POPULATIONS

8.1 Pregnancy

Risk Summary

All pregnancies have a risk of birth defect, loss, or other adverse outcomes. In the U.S. general population, the estimated background risk of major birth defects and miscarriage in clinically recognized pregnancies is 2% to 4% and 15% to 20%, respectively.

Available data from a pregnancy registry do not suggest an increased risk of major birth defects and miscarriage in individuals who received FLUARIX (see Data). Data from women vaccinated with FLUARIX QUADRIVALENT are applicable to FLUARIX because both vaccines are manufactured using the same process and have overlapping compositions.

A developmental toxicity study was performed in female rats administered FLUARIX prior to mating and during gestation. The dose was 0.1 mL on each of 5 occasions (a single human dose is 0.5 mL). The study revealed no evidence of impaired female fertility or harm to the fetus due to FLUARIX (see Data).

Clinical Considerations

Disease-Associated Maternal and/or Embryo/Fetal Risk: Pregnant women infected with seasonal influenza are at increased risk of severe illness associated with influenza infection compared with non-pregnant women. Pregnant women with influenza may be at increased risk for adverse pregnancy outcomes, including preterm labor and delivery.

Data

Human Data: A pregnancy exposure registry (2014 to 2019) included 437 prospective reports of exposure to FLUARIX QUADRIVALENT or FLUARIX, in the United States. After excluding pregnancies lost to follow-up (n = 322), those with an unknown outcome (n = 5), and those ongoing at time of last contact (n = 26), there were 84 pregnancies with exposure within 28 days prior to conception or during pregnancy and with known outcomes which included 1 spontaneous abortion, 1 stillbirth and 3 major birth defects. Among the 84 reports with known pregnancy outcomes, 17 individuals were exposed to FLUARIX QUADRIVALENT in the first trimester with 1 spontaneous abortion with no apparent birth defect and 1 stillbirth with no apparent birth defect reported; 34 individuals were exposed to FLUARIX QUADRIVALENT in the second trimester with 3 major birth defects reported; 21 individuals were exposed to FLUARIX QUADRIVALENT in the third trimester with no major birth defects reported; and 12 individuals were exposed to FLUARIX QUADRIVALENT at an unknown time in pregnancy with no major birth defects reported.

Animal Data: In a developmental toxicity study, the effect of FLUARIX on embryo-fetal and pre-weaning development was evaluated in pregnant rats. Animals were administered FLUARIX by intramuscular injection once prior to gestation, and during the period of organogenesis (gestation Days 6, 8, 11, and 15), 0.1 mL/rat/occasion. No adverse effects on mating, female fertility, pregnancy, parturition, lactation parameters, and embryo-fetal or pre-weaning development were observed. There were no vaccine-related fetal malformations or other evidence of teratogenesis.

8.2 Lactation

Risk Summary

It is not known whether FLUARIX is excreted in human milk. Data are not available to assess the effects of FLUARIX on the breastfed infant or on milk production/excretion. The developmental and health benefits of breastfeeding should be considered along with the mother’s clinical need for FLUARIX and any potential adverse effects on the breastfed child from FLUARIX or from the underlying maternal condition. For preventive vaccines, the underlying maternal condition is susceptibility to disease prevented by the vaccine.

8.4 Pediatric Use

Safety and effectiveness of FLUARIX in children younger than 6 months have not been established.

8.5 Geriatric Use

A randomized, single-blind, active-controlled trial evaluated immunological non‑inferiority in a cohort of subjects aged 65 years and older who received FLUARIX (N = 606) or another U.S.‑licensed trivalent, inactivated influenza vaccine (N = 604) (Sanofi Pasteur SA). In subjects receiving FLUARIX or the comparator vaccine, geometric mean antibody titers (GMTs) post‑vaccination were lower in geriatric subjects than in younger subjects (aged 18 through 64 years). FLUARIX was non‑inferior to the comparator vaccine for each of the 3 influenza strains based on mean antibody titers and seroconversion rates. [See Clinical Studies (14.2).] Solicited local and general adverse events were similar for FLUARIX and the comparator vaccine among geriatric subjects (Table 3). For both vaccines, the frequency of solicited events in subjects aged 65 years and older was lower than in younger subjects (Table 3). [See Adverse Reactions (6.1).]

11 DESCRIPTION

FLUARIX, Influenza Vaccine, is a sterile colorless and slightly opalescent injectable suspension for intramuscular use. FLUARIX is a vaccine prepared from influenza viruses propagated in embryonated chicken eggs. Each of the influenza viruses is produced and purified separately. After harvesting the virus-containing fluids, each influenza virus is concentrated and purified by zonal centrifugation using a linear sucrose density gradient solution containing detergent to disrupt the viruses. Following dilution, the vaccine is further purified by diafiltration. Each influenza virus solution is inactivated by the consecutive effects of sodium deoxycholate and formaldehyde leading to the production of a “split virus.” Each split inactivated virus is then suspended in sodium phosphate-buffered isotonic sodium chloride solution. The vaccine is formulated from the 3 split inactivated virus solutions.

FLUARIX has been standardized according to U.S. Public Health Service (USPHS) requirements for the 2025‑2026 influenza season and is formulated to contain 45 micrograms (mcg) hemagglutinin (HA) per 0.5‑mL dose, in the recommended ratio of 15 mcg HA of each of the following 3 strains: A/Victoria/4897/2022 (H1N1) IVR‑238, A/Croatia/10136RV/2023 (H3N2) X‑425A, and B/Austria/1359417/2021 BVR‑26 (B‑Victoria lineage).

FLUARIX is formulated without preservatives. FLUARIX does not contain thimerosal. Each 0.5‑mL dose also contains octoxinol-10 (TRITON X-100) ≤0.085 mg, α-tocopheryl hydrogen succinate ≤0.1 mg, and polysorbate 80 (Tween 80) ≤0.415 mg. Each dose may also contain residual amounts of hydrocortisone ≤0.0015 mcg, gentamicin sulfate ≤0.15 mcg, ovalbumin ≤0.05 mcg, formaldehyde ≤5 mcg, and sodium deoxycholate ≤50 mcg from the manufacturing process.

The tip cap and rubber plunger stopper of the prefilled syringe are not made with natural rubber latex.

12 CLINICAL PHARMACOLOGY

12.1 Mechanism of Action

Specific levels of hemagglutination-inhibition (HI) antibody titer post-vaccination with inactivated influenza virus vaccines have not been correlated with protection from influenza illness but the HI antibody titers have been used as a measure of vaccine activity. In some human challenge trials, HI antibody titers of ≥1:40 have been associated with protection from influenza illness in up to 50% of subjects.^1,2 Antibody against one influenza virus type or subtype confers little or no protection against another virus. Furthermore, antibody to one antigenic variant of influenza virus might not protect against a new antigenic variant of the same type or subtype. Frequent development of antigenic variants through antigenic drift is the virological basis for seasonal epidemics and the reason for the usual replacement of one or more new strains in each year’s influenza vaccine.

13 NONCLINICAL TOXICOLOGY

13.1 Carcinogenesis, Mutagenesis, Impairment of Fertility

FLUARIX has not been evaluated for carcinogenic or mutagenic potential or for impairment of fertility in males.

14 CLINICAL STUDIES

14.1 Efficacy against Influenza

Efficacy Trial in Adults

The efficacy of FLUARIX was evaluated in Trial 3, a randomized, double-blind, placebo-controlled trial conducted in 2 European countries during the 2006-2007 influenza season. Efficacy of FLUARIX, containing A/New Caledonia/20/1999 (H1N1), A/Wisconsin/67/2005 (H3N2), and B/Malaysia/2506/2004 influenza strains, was defined as the prevention of culture-confirmed influenza A and/or B cases, for vaccine antigenically matched strains, compared with placebo. Healthy subjects aged 18 through 64 years (mean: 39.9 years) were randomized (2:1) to receive FLUARIX (N = 5,103) or placebo (N = 2,549) and monitored for influenza-like illnesses (ILI) starting 2 weeks post-vaccination and lasting for approximately 7 months. In the overall population, 60% of subjects were female and 99.9% were white. Culture-confirmed influenza was assessed by active and passive surveillance of ILI. Influenza-like illness was defined as at least one general symptom (fever ≥100°F and/or myalgia) and at least one respiratory symptom (cough and/or sore throat). After an episode of ILI, nose and throat swab samples were collected for analysis; attack rates and vaccine efficacy were calculated (Table 6).

Table 6. FLUARIX: Attack Rates and Vaccine Efficacy against Culture-Confirmed Influenza A and/or B in Adults Aged 18 through 64 Yearsa (Total Vaccinated Cohort)
 |  |  | Attack Rates (n/N) | Vaccine Efficacy
 | N | n | % | % | Lower Limit | Upper Limit
Antigenically Matched Strainsb
FLUARIX | 5,103 | 49 | 1.0 | 66.9c | 51.9 | 77.4
Placebo | 2,549 | 74 | 2.9 | – | – | –
All Culture-Confirmed Influenza (Matched, Unmatched, and Untyped)d
FLUARIX | 5,103 | 63 | 1.2 | 61.6c | 46.0 | 72.8
Placebo | 2,549 | 82 | 3.2 | – | – | –
a Trial 3: NCT00363870.
b There were no vaccine matched culture-confirmed cases of A/New Caledonia/20/1999 (H1N1) or B/Malaysia/2506/2004 influenza strains with FLUARIX or placebo.
c Vaccine efficacy for FLUARIX exceeded a pre-defined threshold of 35% for the lower limit of the 2-sided 95% CI.
d Of the 22 additional cases, 18 were unmatched and 4 were untyped; 15 of the 22 cases were A (H3N2) (11 cases with FLUARIX and 4 cases with placebo).

In a post-hoc, exploratory analysis by age, vaccine efficacy (against culture-confirmed influenza A and/or B cases, for vaccine antigenically matched strains) in subjects aged 18 through 49 years was 73.4% (95% CI: 59.3, 82.8) [number of influenza cases: FLUARIX (n = 35/3,602) and placebo (n = 66/1,810)]. In subjects aged 50 through 64 years, vaccine efficacy was 13.8% (95% CI: ‑137.0, 66.3) [number of influenza cases: FLUARIX (n = 14/1,501) and placebo (n = 8/739)]. As the trial lacked statistical power to evaluate efficacy within age subgroups, the clinical significance of these results is unknown.

Efficacy Trial in Children

The efficacy of FLUARIX QUADRIVALENT was evaluated in Trial 5, a randomized, observer‑blind, non-influenza vaccine-controlled trial conducted in 13 countries in Asia, Europe, and Central America during the 2011-2012 and 2012-2013 Northern Hemisphere influenza seasons, and from 2012 to 2014 during influenza seasons in subtropical countries. Healthy subjects aged 6 through 35 months (mean age: 22 months) were randomized (1:1) to receive FLUARIX QUADRIVALENT (n = 6,006) or a non-influenza control vaccine (n = 6,012). In the overall population, 51% were male; 27% were white, 45% were Asian, and 28% were of other racial/ethnic groups. Children aged 12 months and older with no history of influenza vaccination and children younger than 12 months received 2 doses of FLUARIX QUADRIVALENT or the Non-Influenza Active Comparator vaccine approximately 28 days apart. Children aged 12 months and older with a history of influenza vaccination received 1 dose. Data for FLUARIX QUADRIVALENT are relevant to FLUARIX because both vaccines are manufactured using the same process and have overlapping compositions.

The influenza virus strain composition of FLUARIX QUADRIVALENT administered in each of the 5 study cohorts followed the World Health Organization (WHO) recommendations (which included 2nd B strain from 2012 onwards) for each influenza season associated with a particular cohort.

Efficacy of FLUARIX QUADRIVALENT was assessed for the prevention of reverse transcriptase polymerase chain reaction (RT-PCR)-confirmed influenza A and/or B disease, due to any seasonal influenza strain, compared with non-influenza control vaccines. Influenza disease included episodes of influenza-like illness (ILI, i.e., fever ≥100.4°F with any of the following: cough, runny nose, nasal congestion, or breathing difficulty) or a consequence of influenza virus infection (acute otitis media or lower respiratory illnesses). Among subjects with RT-PCR-positive influenza A and/or B disease, subjects were further prospectively classified based on the presence of adverse outcomes associated with influenza infection: fever >102.2°F, physician-diagnosed acute otitis media, physician-diagnosed lower respiratory tract illness, physician-diagnosed serious extra-pulmonary complications, hospitalization in the intensive care unit, or supplemental oxygen required for more than 8 hours. Subjects were monitored for influenza disease by passive and active surveillance starting 2 weeks post-vaccination and lasting for approximately 6 months. After an episode of ILI, lower respiratory illness, or acute otitis media, nasal swabs were collected and tested for influenza A and/or B by RT-PCR. All RT-PCR-positive specimens were further tested in cell culture and by antigenic characterization to determine whether the viral strains matched those in the vaccine. Vaccine efficacy for subjects with RT-PCR confirmed and culture-confirmed vaccine matching strains (According-to-Protocol (ATP) cohort for efficacy – time to event) is presented in Table 7.

Table 7. Attack Rates and Vaccine Efficacy against Influenza A and/or B in Children Aged 6 through 35 Monthsa (ATP Cohort for Efficacy – Time to Event)
 | Nb | nc | Attack Rates (n/N) | Vaccine Efficacy
 | Nb | nc | % | % | Lower Limit | Upper Limit
All RT-PCR-Confirmed Influenza
FLUARIX QUADRIVALENT | 5,707 | 344 | 6.03 | 49.8 | 41.8d | 56.8
Non-Influenza Comparatore,f | 5,697 | 662 | 11.62 | - | - | -
All Culture-Confirmed Influenza
FLUARIX QUADRIVALENT | 5,707 | 303 | 5.31 | 51.2 | 44.1g | 57.6
Non-Influenza Comparatore,f | 5,697 | 602 | 10.57 | - | - | -
All Antigenically Matched Culture-Confirmed Influenza
FLUARIX QUADRIVALENT | 5,707 | 88 | 1.54 | 60.1 | 49.1h | 69.0
Non-Influenza Comparatore,f | 5,697 | 216 | 3.79 | - | - | -
ATP = According‑to‑Protocol; RT-PCR = Reverse Transcriptase Polymerase Chain Reaction.
a Trial 5: NCT01439360.
b Number of subjects in the ATP cohort for efficacy – time to event, which included subjects who met all eligibility criteria, who were followed for efficacy and complied with the study protocol until the influenza-like episode.
c Number of subjects who reported at least one case in the reporting period.
d Vaccine efficacy for FLUARIX QUADRIVALENT met the pre-defined criterion for the lower limit of the 2-sided 97.5% CI (>15% for all influenza).
e Children younger than 12 months: pneumococcal 13-valent conjugate vaccine [Diphtheria CRM197 Protein] (Wyeth Pharmaceuticals, Inc.).
f Children 12 months and older: HAVRIX (Hepatitis A Vaccine) for those with a history of influenza vaccination; or HAVRIX (Dose 1) and a varicella vaccine (U.S. Licensed Manufactured by Merck & Co., Inc. or Non-U.S. Licensed Manufactured by GlaxoSmithKline Biologicals) (Dose 2) for those with no history of influenza vaccination.
g Vaccine efficacy for FLUARIX QUADRIVALENT met the pre-defined criterion of >10% for the lower limit of the 2-sided 95% CI.
h Vaccine efficacy for FLUARIX QUADRIVALENT met the pre-defined criterion of >15% for the lower limit of the 2-sided 95% CI.

The vaccine efficacy against RT-PCR-confirmed influenza associated with adverse outcomes was 64.6% (97.5% CI 53.2%, 73.5%). The vaccine efficacy against RT-PCR-confirmed influenza associated with adverse outcomes due to A/H1N1, A/H3N2, B/Victoria, and B/Yamagata was 71.4% (95% CI 48.5%, 85.2%), 51.3% (95% CI 32.7%, 65.2%), 86.7% (95% CI 52.8%, 97.9%), and 68.9% (95% CI 50.6%, 81.2%), respectively.

For RT-PCR-confirmed influenza cases associated with adverse outcomes, the incidence of the specified adverse outcomes is presented in Table 8.

Table 8 . Incidence of Adverse Outcomes Associated with RT-PCR-Positive Influenza in Children Aged 6 through 35 Monthsa (ATP Cohort for Efficacy- Time to Event)b
Influenza-Associated Symptome | FLUARIX QUADRIVALENT; n = 5,707 |  |  | Non-Influenza Active Comparatorc,d; n = 5,697
Influenza-Associated Symptome | Number of Events | Number of Subjectsf | % | Number of Events | Number of Subjectsf | %
Fever >102.2°F/39°C | 62 | 61 | 1.1 | 184 | 183 | 3.2
Acute otitis media (AOM)g | 5 | 5 | 0.1 | 15 | 15 | 0.3
Physician-diagnosed lower respiratory tract illnessh | 28 | 28 | 0.5 | 62 | 61 | 1.1
Physician-diagnosed serious extra-pulmonary complicationsi | 2 | 2 | 0 | 3 | 3 | 0.1
Hospitalization in the intensive care unit | 0 | 0 | 0 | 0 | 0 | 0
Supplemental oxygen required for more than 8 hours | 0 | 0 | 0 | 0 | 0 | 0
ATP = According‑to‑Protocol; RT-PCR = Reverse transcriptase polymerase chain reaction.
a Trial 5: NCT01439360.
b Number of subjects in the ATP cohort for efficacy – time to event, which included subjects who met all eligibility criteria, who were followed for efficacy and complied with the study protocol until the influenza-like episode.
c Children younger than 12 months: pneumococcal 13-valent conjugate vaccine [Diphtheria CRM197 Protein] (Wyeth Pharmaceuticals, Inc.).
d Children 12 months and older: HAVRIX (Hepatitis A Vaccine) for those with a history of influenza vaccination; or HAVRIX (Dose 1) and a varicella vaccine (U.S. Licensed Manufactured by Merck & Co., Inc. or Non-U.S. Licensed Manufactured by GlaxoSmithKline Biologicals) (Dose 2) for those with no history of influenza vaccination.
e Subjects who experienced more than one adverse outcome, each outcome was counted in the respective category.
f Number of subjects with at least one event in a given category.
g Analyses considered AOM cases confirmed by otoscopy.
h Pneumonia, lower respiratory tract infection, bronchiolitis, bronchitis, or croup infection as per final diagnosis by physician.
i Includes myositis, encephalitis or other neurologic condition including seizure, myocarditis/pericarditis or other serious medical condition as per final diagnosis by physician.

14.2 Immunological Evaluation

In Trial 2, a randomized, single-blind, active-controlled U.S. trial, immunological non-inferiority of FLUARIX (N = 923) was compared with FLUZONE (N = 922), a U.S.‑licensed trivalent, inactivated influenza vaccine (Sanofi Pasteur SA). Subjects aged 18 through 64 years and 65 years and older were evaluated for immune responses to each of the vaccine antigens 21 days following vaccination [see Use in Specific Populations (8.5)]. In the overall population, 59% of subjects were female and 91% were white. The co-primary immunogenicity endpoints were GMTs of serum HI antibodies and the percentage of subjects who achieved seroconversion, defined as at least a 4-fold increase in serum HI titer over baseline to ≥1:40, following vaccination. The primary immunogenicity analyses were performed on the According-to-Protocol (ATP) cohort which included all eligible and evaluable subjects with results of at least one serological assay. For each of the influenza antigens, the GMTs and the percentage of subjects who achieved seroconversion are presented in Table 9. FLUARIX was non-inferior to the comparator influenza vaccine based on antibody GMTs (upper limit of the 2‑sided 95% CI for the GMT ratio [comparator influenza vaccine/FLUARIX] ≤1.5) and seroconversion rates (upper limit of the 2-sided 95% CI on difference of the comparator influenza vaccine minus FLUARIX ≤10%).

Table 9. Immune Responses 21 Days after Vaccination with FLUARIX Compared with Comparator Influenza Vaccine in Adults Aged 18 Years and Oldera (ATP Cohort)
 | FLUARIX; n = 858 to 866; (95% CI) |  | Comparator; Influenza Vaccine; n = 846 to 854; (95% CI)
GMTs | Pre-Vaccination | Post-Vaccination | Pre-Vaccination | Post-Vaccination
Anti‑H1 | 27.9; (25.6, 30.5) | 138.0; (125.2, 152.1) | 29.1; (26.6, 31.7) | 92.0; (84.5, 100.3)
Anti‑H3 | 16.3; (15.1, 17.6) | 121.6; (110.5, 133.7) | 16.5; (15.4, 17.6) | 114.0; (104.4, 124.5)
Anti‑B | 47.7; (44.1, 51.6) | 231.9; (215.4, 249.6) | 54.1; (49.9, 58.6) | 273.7; (253.4, 295.7)
Seroconversionb | % (95% CI); Post-Vaccination |  | % (95% CI); Post-Vaccination
A/New Caledonia/20/99 (H1N1) | 45.7; (42.3, 49.1) |  | 33.8; (30.6, 37.1)
A/New York/55/2004 (H3N2) | 67.1; (63.9, 70.3) |  | 65.5; (62.2, 68.7)
B/Jiangsu/10/2003 | 52.7; (49.3, 56.1) |  | 53.8; (50.4, 57.2)
Comparator influenza vaccine manufactured by Sanofi Pasteur SA.
ATP = According‑to‑protocol; GMT = Geometric mean antibody titer; CI = Confidence Interval; H1 = A/New Caledonia/20/99 (H1N1); H3 = A/New York/55/2004 (H3N2) for FLUARIX and A/California/7/2004 (H3N2) for comparator influenza vaccine; B = B/Jiangsu/10/2003.
ATP cohort included all eligible and evaluable subjects with results of at least one serological assay.
a Trial 2: NCT00197288.
b Seroconversion defined as at least a 4-fold increase in serum titers of HI antibodies to ≥1:40.

14.3 Concomitant Administration with Zoster Vaccine Recombinant, Adjuvanted (SHINGRIX)

In an open-label, randomized clinical trial (NCT01954251) in adults aged 50 years and older, there was no evidence for interference in antibody responses (HI antibodies and anti-gE antibodies) to FLUARIX QUADRIVALENT or the coadministered vaccine, SHINGRIX [see Adverse Reactions (6.1)].

15 REFERENCES

1. Hannoun C, Megas F, Piercy J. Immunogenicity and protective efficacy of influenza vaccination. Virus Res. 2004;103:133-138.
2. Hobson D, Curry RL, Beare AS, et al. The role of serum haemagglutination-inhibiting antibody in protection against challenge infection with influenza A2 and B viruses. J Hyg Camb. 1972;70:767-777.

16 HOW SUPPLIED/STORAGE AND HANDLING

FLUARIX is supplied in 0.5-mL single-dose, disposable, prefilled TIP‑LOK syringes (Luer Lock syringes) packaged without needles. TIP-LOK syringes are to be used with Luer Lock compatible needles. The tip cap and rubber plunger stopper of the prefilled syringe are not made with natural rubber latex.

NDC 58160-912-41 Syringe in Package of 10: NDC 58160-912-52

Store refrigerated between 2º and 8ºC (36º and 46ºF). Do not freeze. Discard if the vaccine has been frozen. Store in the original package to protect from light.

17 PATIENT COUNSELING INFORMATION

Provide the following information to the vaccine recipient or guardian:

- Inform of the potential benefits and risks of immunization with FLUARIX.
- Educate regarding potential side effects, emphasizing that: (1) FLUARIX contains non‑infectious killed viruses and cannot cause influenza and (2) FLUARIX is intended to provide protection against illness due to influenza viruses only, and cannot provide protection against all respiratory illness.
- Give the Vaccine Information Statements, which are required by the National Childhood Vaccine Injury Act of 1986 to be given prior to each immunization. These materials are available free of charge at the Centers for Disease Control and Prevention (CDC) website (www.cdc.gov/vaccines).
- Instruct that annual revaccination is recommended.

FLUARIX, TIP-LOK, and HAVRIX are registered trademarks of the GSK group of companies. The other brands listed are trademarks of their respective owners and are not trademarks of the GSK group of companies. The makers of these brands are not affiliated with and do not endorse the GSK group of companies or its products.

Manufactured by GlaxoSmithKline Biologicals, Dresden, Germany,

a branch of SmithKline Beecham Pharma GmbH & Co. KG, Munich, Germany

Licensed by GlaxoSmithKline Biologicals, Rixensart, Belgium, US License 1617

Distributed by GlaxoSmithKline, Durham, NC 27701

©2025 the GSK group of companies or its licensor.

FLX:22PI

PACKAGE LABEL

PRINCIPAL DISPLAY PANEL

NDC 58160-912-52

FLUARIX

Influenza Vaccine

2025/2026 Formula

Rx only

GSK

For 6 Months of Age and Older

10 Disposable Single-Dose Prefilled TIP-LOK Syringes each containing one 0.5-mL dose

TIP-LOK syringes to be used with Luer Lock compatible needles

NEEDLES NOT INCLUDED

Fluarix

Made in Germany

©2025 GSK group of companies or its licensor.

Rev. 3/25

523645